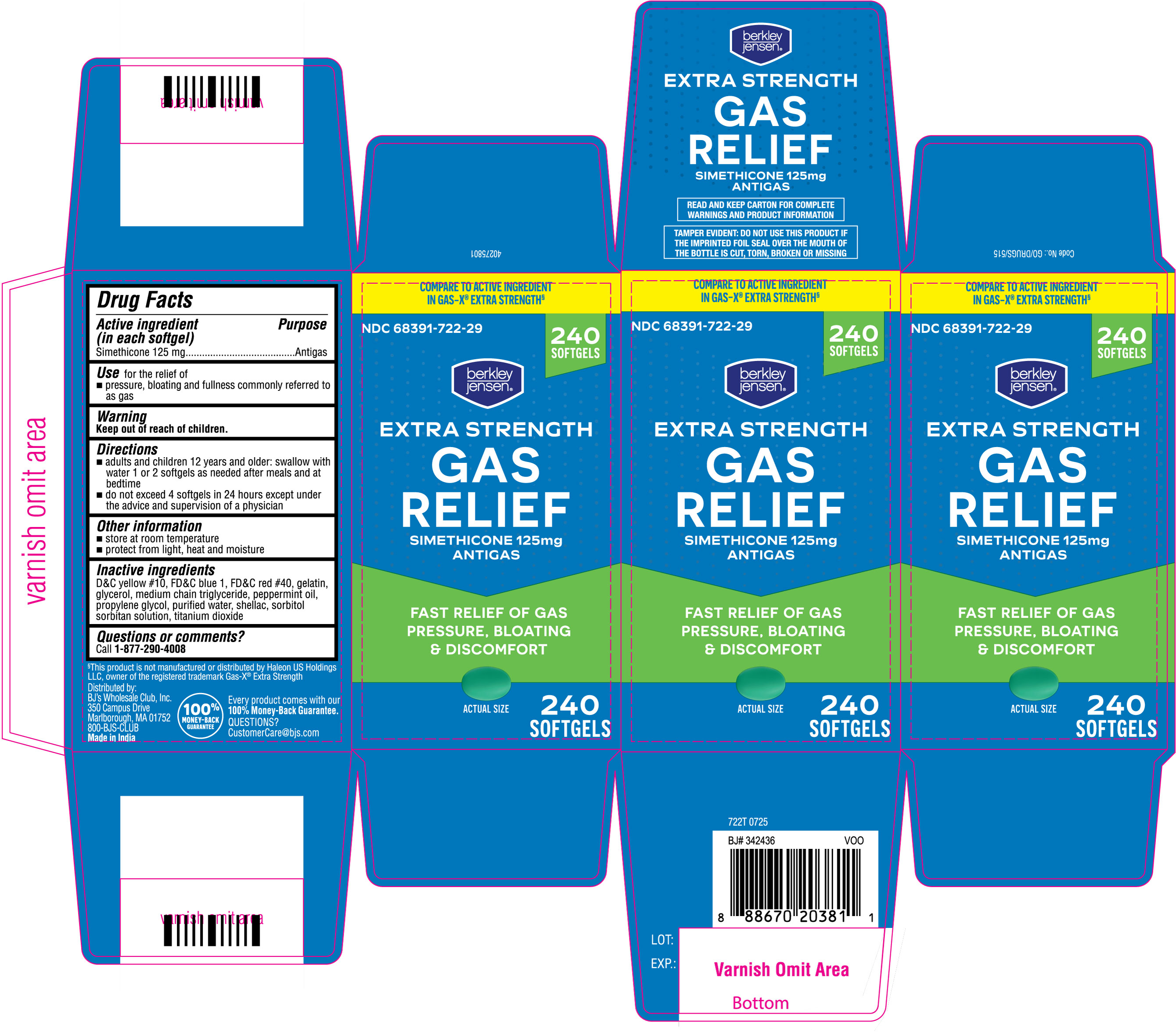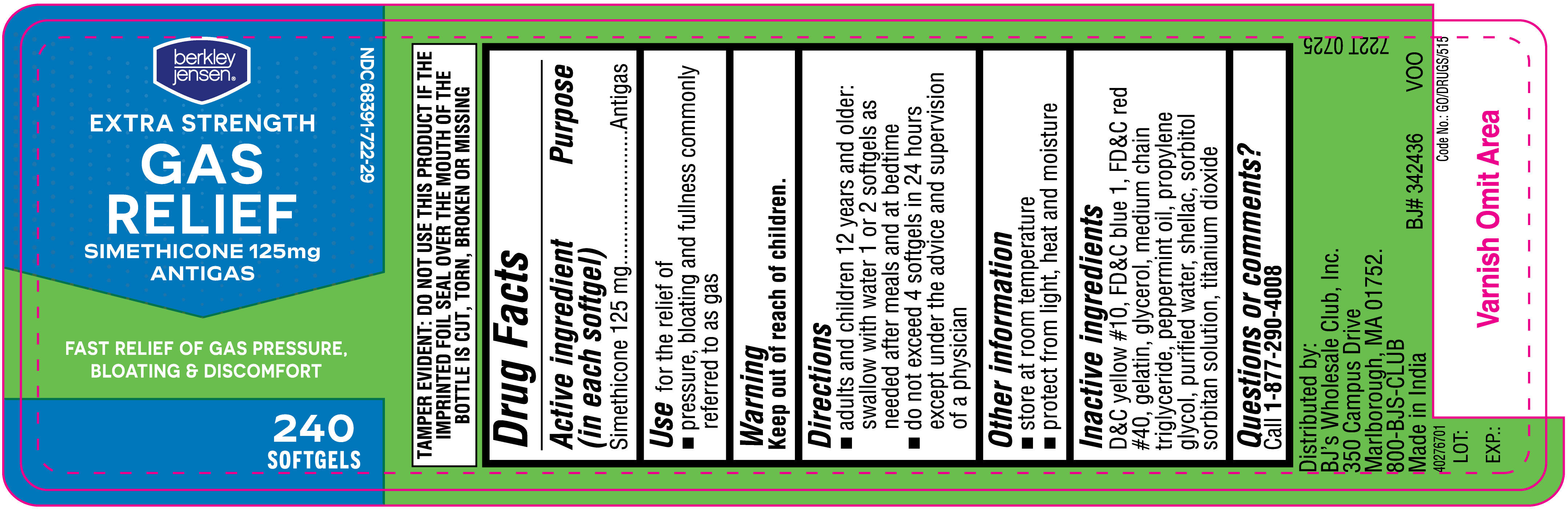 DRUG LABEL: Gas Relief
NDC: 68391-722 | Form: CAPSULE
Manufacturer: BJWC (Berkley & Jensen / BJ's)
Category: otc | Type: HUMAN OTC DRUG LABEL
Date: 20250819

ACTIVE INGREDIENTS: DIMETHICONE 125 mg/1 1
INACTIVE INGREDIENTS: FD&C RED NO. 40; GLYCERIN; TITANIUM DIOXIDE; SORBITOL SOLUTION; WATER; MEDIUM-CHAIN TRIGLYCERIDES; D&C YELLOW NO. 10; GELATIN, UNSPECIFIED; SORBITAN; SHELLAC; FD&C BLUE NO. 1; PROPYLENE GLYCOL; PEPPERMINT OIL

BJs Simethicone Soft Gelatin Capsules 125 mg

Drug Facts

Active ingredient (in each softgel)

Simethicone 125 mg

Purpose

Antigas

INDICATIONS AND USAGE

Use for the relief of

- pressure, bloating and fullness commonly referred to as gas

Warning

Keep out of reach of children.

Directions

- adults and children 12 years and older: swallow with water 1 or 2 softgels as needed after meals and at bedtime
- do not exceed 4 softgels in 24 hours except under the advice and supervision of a physician

Other information

- store at room temperature
- protect from light, heat and moisture

Inactive ingredients

D&C Yellow #10, FD&C blue 1, FD&C red #40, gelatin, glycerol, medium chain triglyceride, peppermint oil, propylene glycol, purified water, shellac, sorbitol sorbitan solution, titanium dioxide

Questions or comments? Call 1-877-290-4008

722T 240ct label

722T 240ct Carton